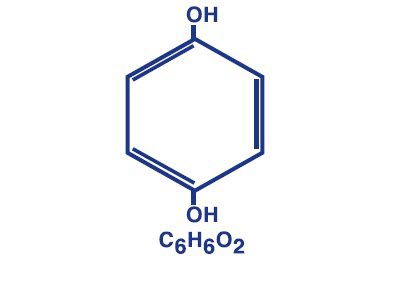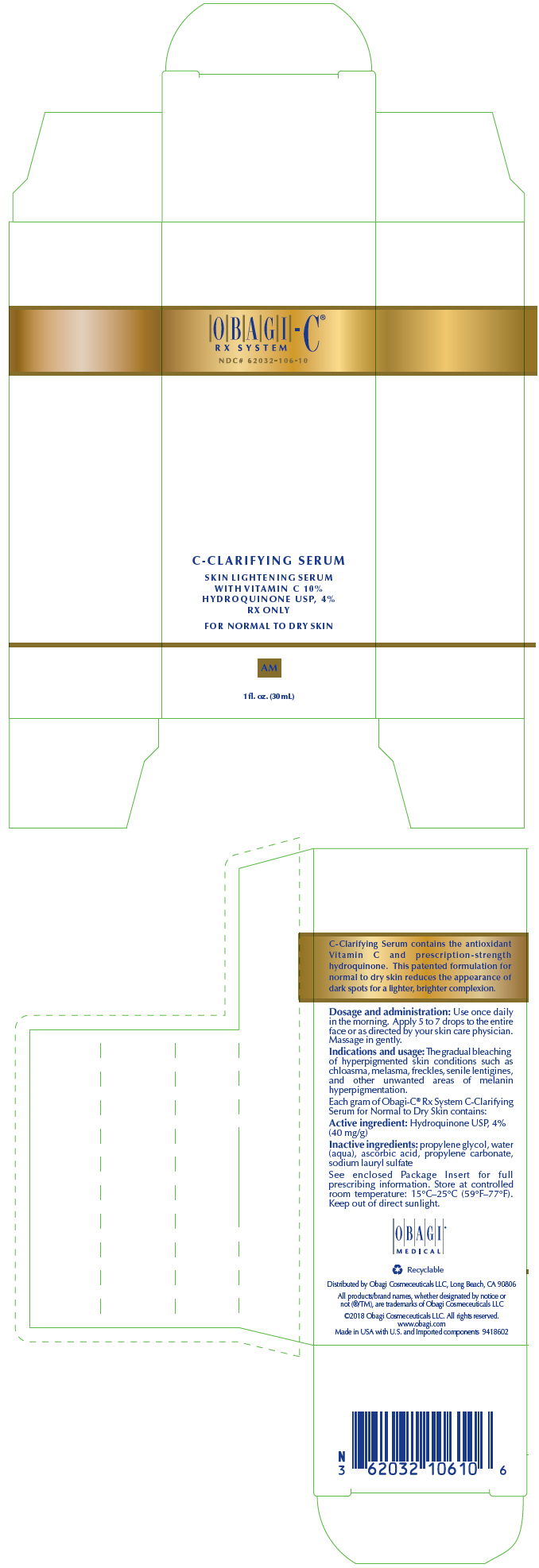 DRUG LABEL: OBAGI C RX system C CLARIFYING SERUM
NDC: 62032-106 | Form: SOLUTION
Manufacturer: Obagi Cosmeceuticals LLC
Category: prescription | Type: HUMAN PRESCRIPTION DRUG LABEL
Date: 20250101

ACTIVE INGREDIENTS: HYDROQUINONE 40 mg/1 mL
INACTIVE INGREDIENTS: ASCORBIC ACID; PROPYLENE CARBONATE; PROPYLENE GLYCOL; SODIUM LAURYL SULFATE; WATER

OBAGI-C®
RX SYSTEM

WELCOME TO THE OBAGI-C® RX SYSTEM OF SKIN CARE PRODUCTS!

PATIENT INFORMATION

For Topical Use Only

Complete skin care regimen formulated with 4% hydroquinone to reduce hyperpigmentation and other essential ingredients to help address the signs of skin aging caused by photoaging.

Please read this product information prior to use of the Obagi-C® Rx System. Any questions regarding your particular skin care regimen should be directed to your physician. More information about the Obagi-C® Rx System or other Obagi systems is available at our website at www.obagi.com.

PHYSICIAN PRESCRIBING INFORMATION

Rx only

FOR EXTERNAL USE ONLY

62032-106-10 Obagi-C® Rx System C-Clarifying Serum for Normal to Dry Skin

Each gram of Obagi-C® Rx System C-Clarifying Serum for Normal to Dry Skin contains:

Active: Hydroquinone, USP 4% (40 mg per g)

Inactives: ascorbic acid, propylene carbonate, propylene glycol, sodium lauryl sulfate, water

62032-122-10 Obagi-C® Rx System C-Clarifying Serum for Normal to Oily Skin

Each gram of Obagi-C® Rx System C-Clarifying Serum for Normal to Oily Skin contains:

Active: Hydroquinone, USP 4% (40 mg per g)

Inactives: ascorbic acid, dipropylene glycol, fragrance, propylene carbonate, propylene glycol, SD alcohol-39-C, sodium lauryl sulfate, water

62032-105-36 Obagi-C® Rx System C-Therapy Night Cream

Each gram of Obagi-C® Rx System C-Therapy Night Cream contains:

Active: Hydroquinone, USP 4% (40 mg per g)

Inactives: ascorbic acid, BHT, cetyl alcohol, disodium EDTA, glycerin, lactic acid, methylparaben, phenyl trimethicone, PPG-2 myristyl ether propionate, propylparaben, saponins, sodium lauryl sulfate, sodium metabisulfite, TEA-salicylate, tocopheryl acetate, water

Description

Hydroquinone is 1,4-benzenediol. Hydroquinone occurs as fine, white needles. The drug is freely soluble in water and in alcohol. Chemically, hydroquinone is designated as p-dihydroxybenzene; the empirical formula is C6H6O2; molecular weight is 110.11 g per mol.

The chemical structure is in the diagram.

CLINICAL PHARMACOLOGY

Topical application of hydroquinone produces a reversible depigmentation of the skin by inhibition of the enzymatic oxidation of tyrosine to 3, 4-dihydroxyphenylalanine (DOPA) and suppression of other melanocyte metabolic processes. Exposure to sunlight or ultraviolet light will cause repigmentation of the bleached areas, which may be prevented by the use of sunscreen agents contained in the Obagi-C® Rx System Sun Shield Matte Broad Spectrum SPF 50.

INDICATIONS AND USAGE

The gradual bleaching of hyperpigmented skin conditions such as chloasma, melasma, freckles, senile lentigines, and other unwanted areas of melanin hyperpigmentation.

DOSAGE AND ADMINISTRATION

A thin application should be applied once or twice daily or as directed by a physician. If no improvement is seen after three (3) months of treatment, use of this product should be discontinued. Sun exposure should be limited by using a sunscreen agent or protective clothing to cover bleached skin when using and after using this product in order to prevent darkening from reoccurring.

WARNINGS

• Hydroquinone is a skin-bleaching agent, which may produce unwanted cosmetic effects if not used as directed. The physician should be familiar with the contents of this insert before prescribing or dispensing this product.

• Test for skin sensitivity before using by applying a small amount to an unbroken patch of skin and check within 24 hours. Minor redness is not a contraindication, but where there is itching or vesicle formation or excessive inflammatory response, the product should be discontinued and a physician consulted. Close patient supervision is recommended.

• Avoid contact with eyes, nose, mouth, and lips. In case of accidental contact, the patient should rinse thoroughly with water and contact a physician.

• Sunscreen use is an essential aspect of hydroquinone therapy because even minimal sunlight exposure sustains melanocytic activity.

The Obagi-C® Rx System C-Therapy Night Cream contains sodium metabisulfite, a sulfite that may cause allergic-type reactions including anaphylactic symptoms and life-threatening or less severe asthmatic episodes in certain susceptible people. The overall prevalence of sulfite sensitivity in the general population is unknown and probably low. Sulfite sensitivity is seen more frequently in asthmatic than in nonasthmatic people.

PRECAUTIONS

(See WARNINGS.)

Treatment should be limited to relatively small areas of the body at one time since some patients experience a transient skin reddening and a mild burning sensation, which does not preclude treatment.

Pregnancy

Pregnancy Category C

Animal reproduction studies have not been conducted with topical hydroquinone. It is also not known whether hydroquinone can cause fetal harm when used topically on a pregnant woman or affect reproductive capacity. It is not known to what degree, if any, topical hydroquinone is absorbed systemically. Topical hydroquinone should be used on pregnant women only when clearly indicated.

Nursing Mothers

It is not known whether topical hydroquinone is absorbed or excreted in human milk. Caution is advised when topical hydroquinone is used by a nursing mother.

Pediatric Usage

Safety and effectiveness in children, below the age of 12 years, have not been established.

ADVERSE REACTIONS

No systemic adverse reactions have been reported. Occasional hypersensitivity (localized contact dermatitis) may occur, in which case the product should be discontinued and physician notified immediately.

To report SUSPECTED ADVERSE REACTIONS, contact Obagi Medical Products, a division of Valeant Pharmaceuticals North America LLC, at 1-800-321-4576 or FDA at 1-800-FDA-1088 or www.fda.gov/medwatch.

CONTRAINDICATIONS

People with prior history of sensitivity or allergic reaction to this product or any of its ingredients should not use it. The safety of topical hydroquinone use during pregnancy or in children (12 years and under) has not been established.

HOW SUPPLIED

Obagi-C® Rx System C-Clarifying Serum
(Hydroquinone, USP 4%) for Normal to Dry Skin is available as follows:
1 fl. oz. (30 mL) bottle
NDC 62032-106-10

Obagi-C® Rx System C-Clarifying Serum
(Hydroquinone, USP 4%) for Normal to Oily Skin is available as follows:
1 fl. oz. (30 mL) bottle
NDC 62032-122-10

Obagi-C® Rx System C-Therapy Night Cream
(Hydroquinone, USP 4%) is available as follows:
Net wt. 2 oz. (57 g) bottle
NDC 62032-105-36

Store at controlled room temperature: 15° to 25°C (59° to 77°F). Keep out of direct sunlight.

Distributed by:

Obagi Medical Products, Inc., a division of Valeant Pharmaceuticals North America LLC
Bridgewater, NJ 08807 USA

U.S. Patent 6,299,889

Obagi-C is a trademark of Valeant Pharmaceuticals International, Inc. or its affiliates.

©OMP, Inc.

www.obagi.com

9578900

Revised: 10/2016

PRINCIPAL DISPLAY PANEL - 30 mL Bottle Carton

OBAGI-C®
RX SYSTEM

NDC# 62032-106-10

C-CLARIFYING SERUM

SKIN LIGHTENING SERUM
WITH VITAMIN C 10%
HYDROQUINONE USP, 4%
RX ONLY

FOR NORMAL TO DRY SKIN

AM

1fl. oz. (30 mL)